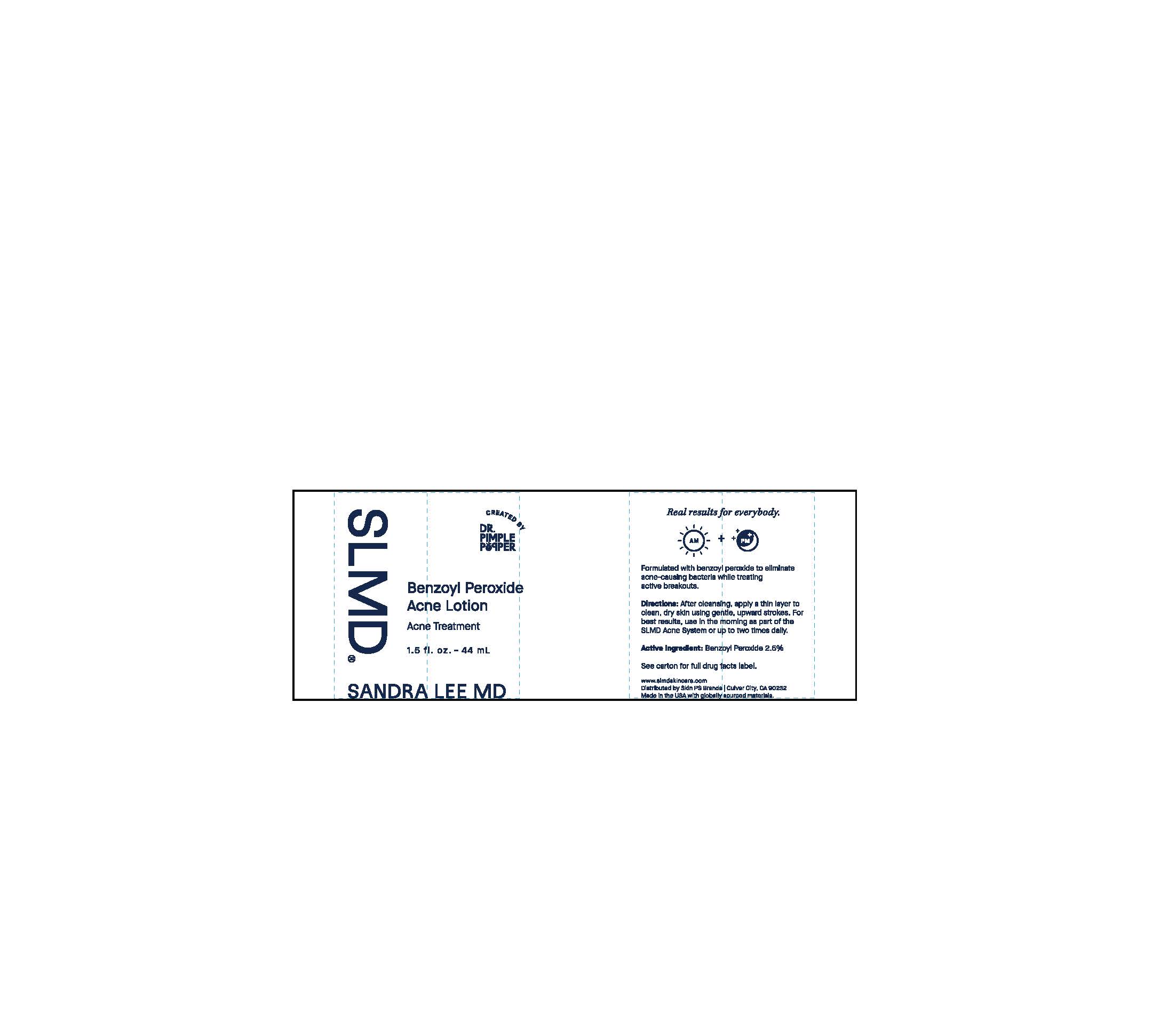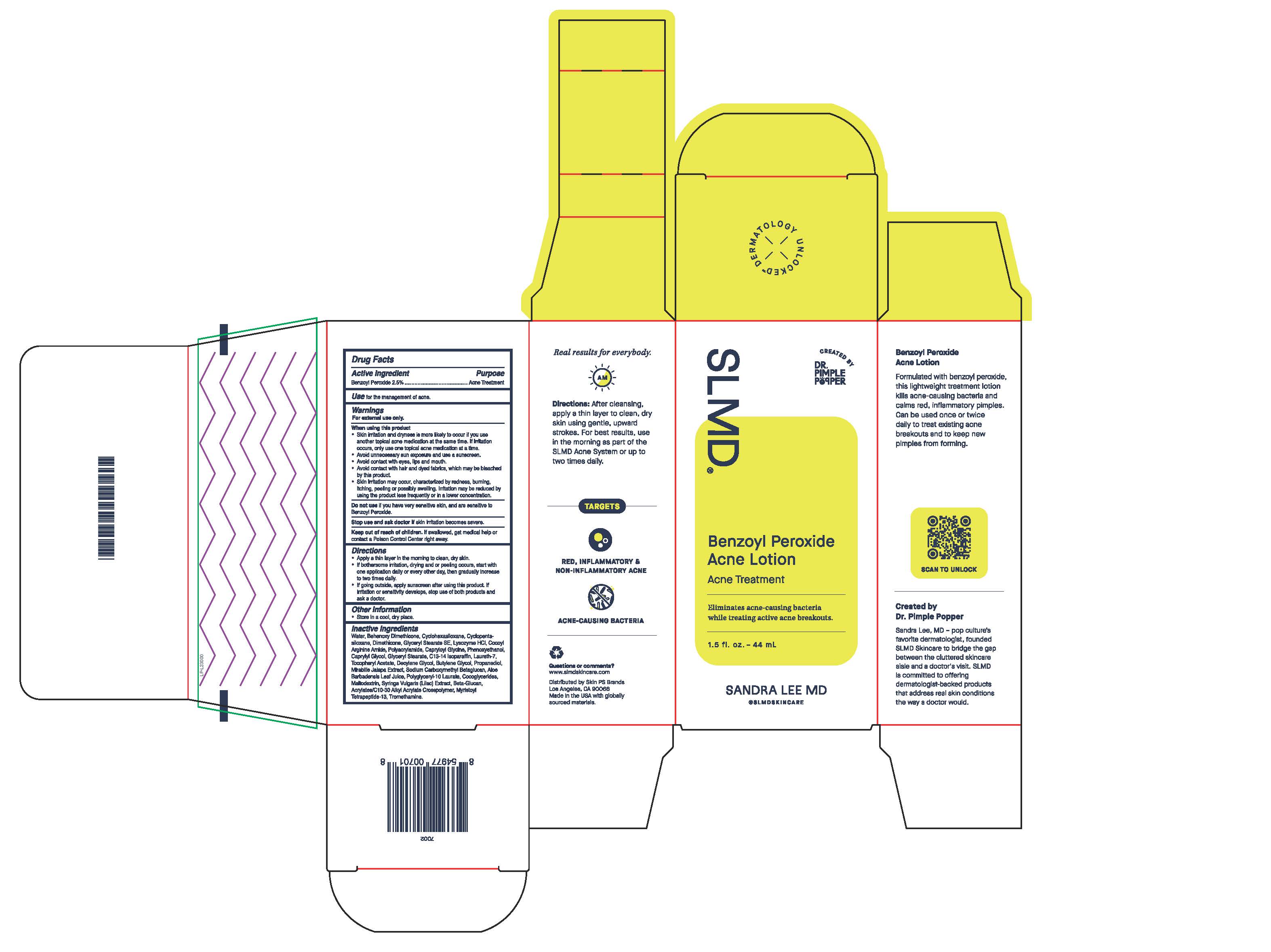 DRUG LABEL: Benzoyl Peroxide Acne
NDC: 73318-7006 | Form: LOTION
Manufacturer: Skin PS Brands
Category: otc | Type: HUMAN OTC DRUG LABEL
Date: 20251230

ACTIVE INGREDIENTS: BENZOYL PEROXIDE 25 mg/1 g
INACTIVE INGREDIENTS: PROPANEDIOL; MIRABILIS JALAPA WHOLE; MALTODEXTRIN; SODIUM CARBOXYMETHYL .BETA.-GLUCAN (DS 0.65-0.85); ACRYLATES/C10-30 ALKYL ACRYLATE CROSSPOLYMER (60000 MPA.S); ARGININE; DIMETHICONE; CYCLOMETHICONE 6; CYCLOMETHICONE 5; GLYCERYL STEARATE SE; SYRINGA VULGARIS WHOLE; ALOE VERA LEAF; WATER; LYSOZYME HYDROCHLORIDE; POLYACRYLAMIDE (1500 MW); CAPRYLOYL GLYCINE; CAPRYLYL GLYCOL; POLYGLYCERYL-10 LAURATE; PHENOXYETHANOL; .ALPHA.-TOCOPHEROL ACETATE; C13-14 ISOPARAFFIN; LAURETH-7 CARBOXYLIC ACID; DECYLENE GLYCOL; MYRISTOYL TETRAPEPTIDE-4; BUTYLENE GLYCOL; SODIUM C14-16 OLEFIN SULFONATE; COCO-GLYCERIDES; TROMETHAMINE

Benzoyl Peroxide Acne Lotion

Active Ingredient

Benzoyl Peroxide 2.5%

Purpose

Acne Treatment

Use

for the management of acne.

Warnings

For external use only.

When using this product

- Skin irritation and dryness is more likely to occur if you use another topical acne medication at the same time. If irritation occurs, only use one topical acne medication at a time.
- Avoid unnecessary sun exposure and use a sunscreen.
- Avoid contact with eyes, lips and mouth.
- Avoid contact with hair and dyed fabrics, which may be bleached by this product.
- Skin irritation may occur, characterized by redness, burning, itching, peeling, or possibly swelling. Irritation may be reduced by using the product less frequently or in a lower concentration.

Do not use

if you have very sensitive skin, and are sensitive to Benzyl Peroxide.

Stop use and ask a doctor if

skin irritation becomes severe.

Keep out of reach of children.

If swallowed, get medical help or contact a Poison Control Center right away.

Directions

- Apply a thin layer in the morning to clean, dry skin.
- If bothersome irritation, drying and or peeling occurs, start with one application daily or every other day, then gradually increase to two times daily.
- If going outside, apply sunscreen after using this product. If irritation or sensitivity develops, stop use of both products and ask a doctor.

Other Information

- Store in a cool, dry place.

Inactive Ingredients

Water, Behenoxy Dimethicone, Cyclohexasiloxane, Cyclopentasiloxane, Dimethicone, Glyceryl Stearate SE, Lysozyme HCl, Cocoyl Arginine Amide, Polyacrylamide, Capryloyl Glycine, Phenoxyethanol, Caprylyl Glycol, Glyceryl Stearate, C13-14 Isoparaffin, Laureth-7, Tocopheryl Acetate, Decylene Glycol, Butylene Glycol, Propanediol, Mirabilis Jalapa Extract, Sodium Carboxymethyl Betaglucan, Aloe Barbadensis Leaf Juice, Polyglyceryl-10 Laurate, Cocoglycerides, Maltodextrin, Syringa Vulgaris (Lilac) Extract, Beta-Glucan, Acrylates/C10-30 Alkyl Acrylate Crosspolymer, Myristoyl Tetrapeptide-13, Tromethamine.

Questions or comments?

www.slmdskincare.com

Distributed by Skin PS Brands

Los Angeles, CA 90066

Made in the USA with globally sourced materials.

SLMD Sandra Lee MD

Created by Dr. Pimple Popper

Benzoyl Peroxide

Acne Lotion

Acne Treatment

Eliminates acne-causing bacteria

while treating active acne breakouts.

1.5 fl. oz. - 44 mL

SANDRA LEE MD

@SLMDSKINCARE

Unit Carton:

Primary:

Real results for everybody.

AM

Directions: After cleansing, apply a thin layer to clean, dry skin using gentle, upward strokes. For best results, use in the morning as part of the SLMD Acne System or up to two times daily.

TARGETS

RED, INFLAMMATORY &

NON-INFLAMMATORY ACNE

ACNE-CAUSING BACTERIA

Questions or comments?

www.slmdskincare.com

Distributed by Skin PS Brands

Los Angeles, CA 90066

Made in the USA with globally sourced materials.